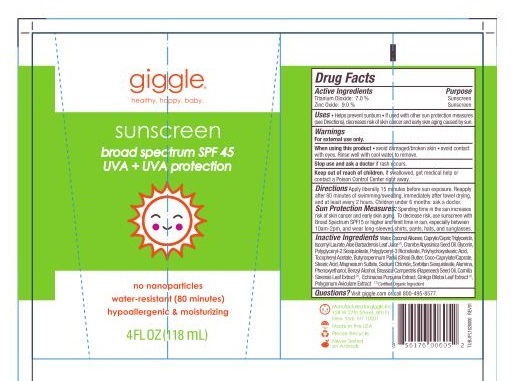 DRUG LABEL: sunscreen
NDC: 70306-5357 | Form: LOTION
Manufacturer: giggle
Category: otc | Type: HUMAN OTC DRUG LABEL
Date: 20151201

ACTIVE INGREDIENTS: ZINC OXIDE 9 g/100 mL; TITANIUM DIOXIDE 7 g/100 mL
INACTIVE INGREDIENTS: SODIUM CHLORIDE; ALCOHOL; BENZYL ALCOHOL; POTASSIUM SORBATE; SODIUM BENZOATE; COCONUT ALKANES; ECHINACEA PURPUREA; MEDIUM-CHAIN TRIGLYCERIDES; POLYGLYCERYL-2 SESQUIISOSTEARATE; POLYGLYCERYL-3 RICINOLEATE; CRAMBE HISPANICA SUBSP. ABYSSINICA SEED OIL; POLYGONUM AVICULARE TOP; ALPHA-TOCOPHEROL ACETATE; SHEA BUTTER; GINKGO; ALUMINUM OXIDE; WATER; ISOAMYL LAURATE; GLYCERIN; ALOE VERA LEAF; POLYHYDROXYSTEARIC ACID (2300 MW); GREEN TEA LEAF; BRASSICA RAPA SUBSP. OLEIFERA OIL; COCO-CAPRYLATE/CAPRATE; MAGNESIUM SULFATE; SORBITAN SESQUIOLEATE; STEARIC ACID; PHENOXYETHANOL

giggle sunscreen for early 2016

Active Ingredients

Active Ingredients | Purpose
Titanium Dioxide: 7.0% | Sunscreen
Zinc Oxide: 9.0% | Sunscreen

Warnings

For external use only.

When using this product - avoid damaged/broken skin - avoid contact with eyes. Rinse well with cool water to remove.

Stop use and ask a doctor if rash occurs.

Keep out of reach of children. If swallowed, get medical help or contact a Poison Control Center right away.

Directions

Directions Apply liberally 15 minutes before sun exposure. Reapply after 80 minutes of swimming/sweating, immediately after towel drying, and at least every 2 hours. Children under 6 months: ask a doctor.

Sun Protection Measures: Spending time in sun increases risk of skin cancer and early skin aging. To decrease risk, use sunscreen with Broad Spectrum SPF 15 or higher and limit time in sun especially 10am-2pm, and wear long-sleeved shirts, pants, hats, sunglasses.

Inactive Ingredients

Inactive Ingredients Water, Coconut Alkanes, Caprylic/Capric Triglyceride, Isoamyl Laurate, Aloe Barbadensis Leaf Juice(1), Crambe Abyssinica Seed Oil, Glycerin, Polyglyceryl-2 Sesquioleate, Polyglyceryl-3 Ricinoleate, Polyhydroxystearic Acid, Tocopheryl Acetate, Butyrospermum Parkii (Shea) Butter, Coco-Caprylate/Caprate, Stearic Acid, Magnesium Sulfate, Sodium Chloride, Sorbitan Sesquioleate, Alumina, Phenoxyethanol, Benzyl Alcohol, Brassica Campestris (Rapeseed) Oil, Camilla Sinesis Leaf Extract(1), Echinacea Purpurea Extract, Ginkgo Biloba Leaf Extract(1), Polygonum Aviculare Extract(1)Certified Organic Ingredient

QUESTIONS

Questions? Visit giggle.com or call 800-495-8577.